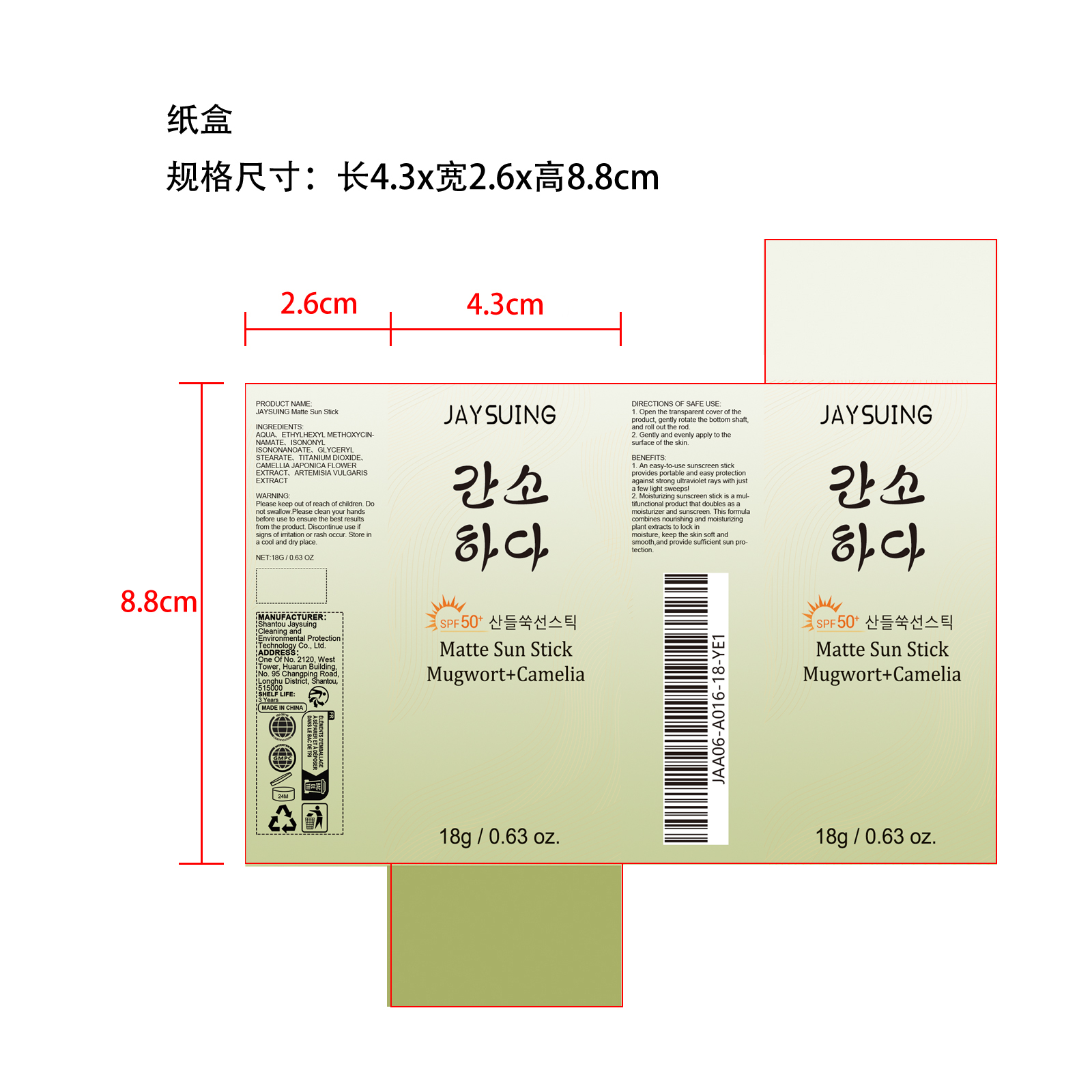 DRUG LABEL: JAYSUING Matte Sun Stick
NDC: 85060-010 | Form: CREAM
Manufacturer: Shantou Jaysuing Cleaning and Environmental Protection Technology Co., Ltd.
Category: otc | Type: HUMAN OTC DRUG LABEL
Date: 20251208

ACTIVE INGREDIENTS: ARTEMISIA VULGARIS OIL 0.036 mg/18 mg; CAMELLIA JAPONICA FLOWER OIL 0.036 mg/18 mg
INACTIVE INGREDIENTS: ETHYLHEXYL METHOXYCINNAMATE 0.9 mg/18 mg; GLYCERYL STEARATE 0.27 mg/18 mg; ISONONYL ISONONANOATE 0.72 mg/18 mg; TITANIUM DIOXIDE 0.18 mg/18 mg; AQUA 15.858 mg/18 mg

ACTIVE INGREDIENT

CAMELLIA JAPONICA FLOWER EXTRACT、ARTEMISIA VULGARIS EXTRACT

PURPOSE

1. An easy-to-use sunscreen stick provides portable and easy protection against strong ultraviolet rays with just a few light sweeps

2. Moisturizing sunscreen stick is a multifunctional product that doubles as a moisturizer and sunscreen. This formula combines nourishing and moisturizing plant extracts to lock in moisture, keep the skin soft and smooth,and provide sufficient sun protection.

WHEN USING

1. Open the transparent cover of the product, gently rotate the bottom shaft, and roll out the rod.

2. Gently and evenly apply to the surface of the skin.

WARNINGS

Please keep out of reach of children. Do not swallow.Please clean your hands before use to ensure the best results from the product. Discontinue use if signs of irritation or rash occur. Store in a cool and dry place.

DO NOT USE

Discontinue use if signs of irritation or rash occur.

STOP USE

Discontinue use if signs of irritation or rash occur.

KEEP OUT OF REACH OF CHILDREN

Please keep out of reach of children. Do not swallow.

STORAGE AND HANDLING

Store in a cool and dry place.

INACTIVE INGREDIENT

AQUA、ETHYLHEXYL METHOXYCINNAMATE、ISONONYL ISONONANOATE、GLYCERYL STEARATE、TITANIUM DIOXIDE

INDICATIONS AND USAGE

1. Open the transparent cover of the product, gently rotate the bottom shaft, and roll out the rod.

2. Gently and evenly apply to the surface of the skin.

DOSAGE AND ADMINISTRATION

1. Open the transparent cover of the product, gently rotate the bottom shaft, and roll out the rod.

2. Gently and evenly apply to the surface of the skin.